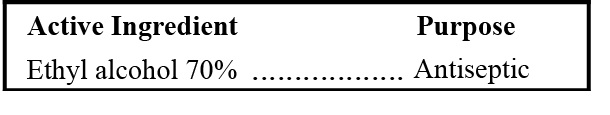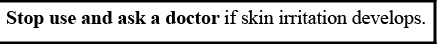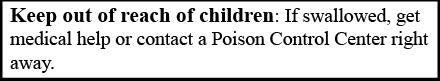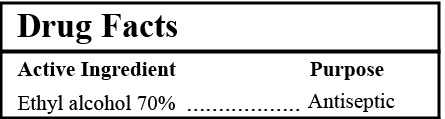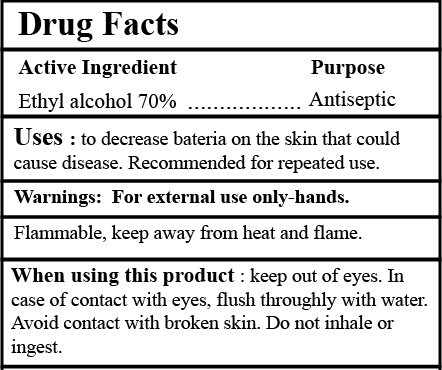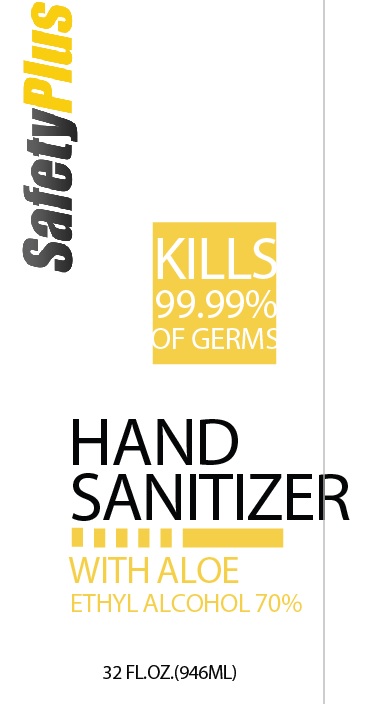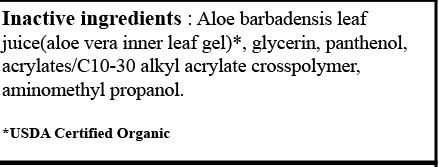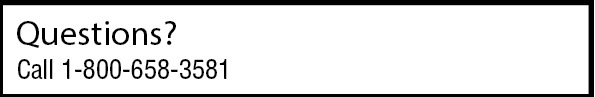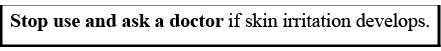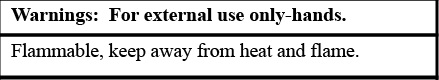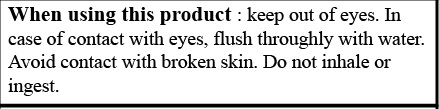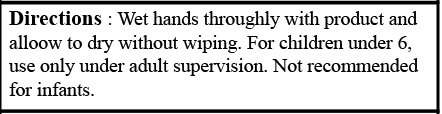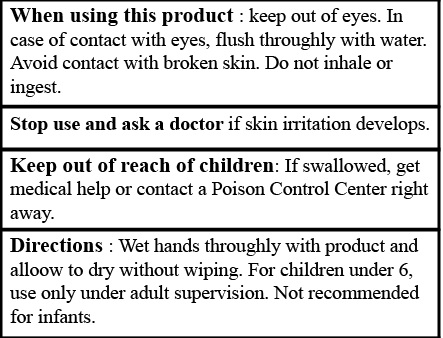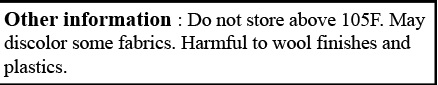 DRUG LABEL: 70% SafetyPlus Hand Sanitizer 32oz
NDC: 80174-109 | Form: GEL
Manufacturer: SafetyPlus, Inc.
Category: otc | Type: HUMAN OTC DRUG LABEL
Date: 20220201

ACTIVE INGREDIENTS: ALCOHOL 70 mL/100 mL
INACTIVE INGREDIENTS: ALOE VERA LEAF 25.1 mL/100 mL; GLYCERIN 4 mL/100 mL; PANTHENOL 0.5 mL/100 mL; CARBOMER COPOLYMER TYPE A 0.3 mL/100 mL; AMINOMETHYLPROPANOL 0.3 mL/100 mL

SafetyPlus Hand Sanitizer with Aloe 70% 32oz